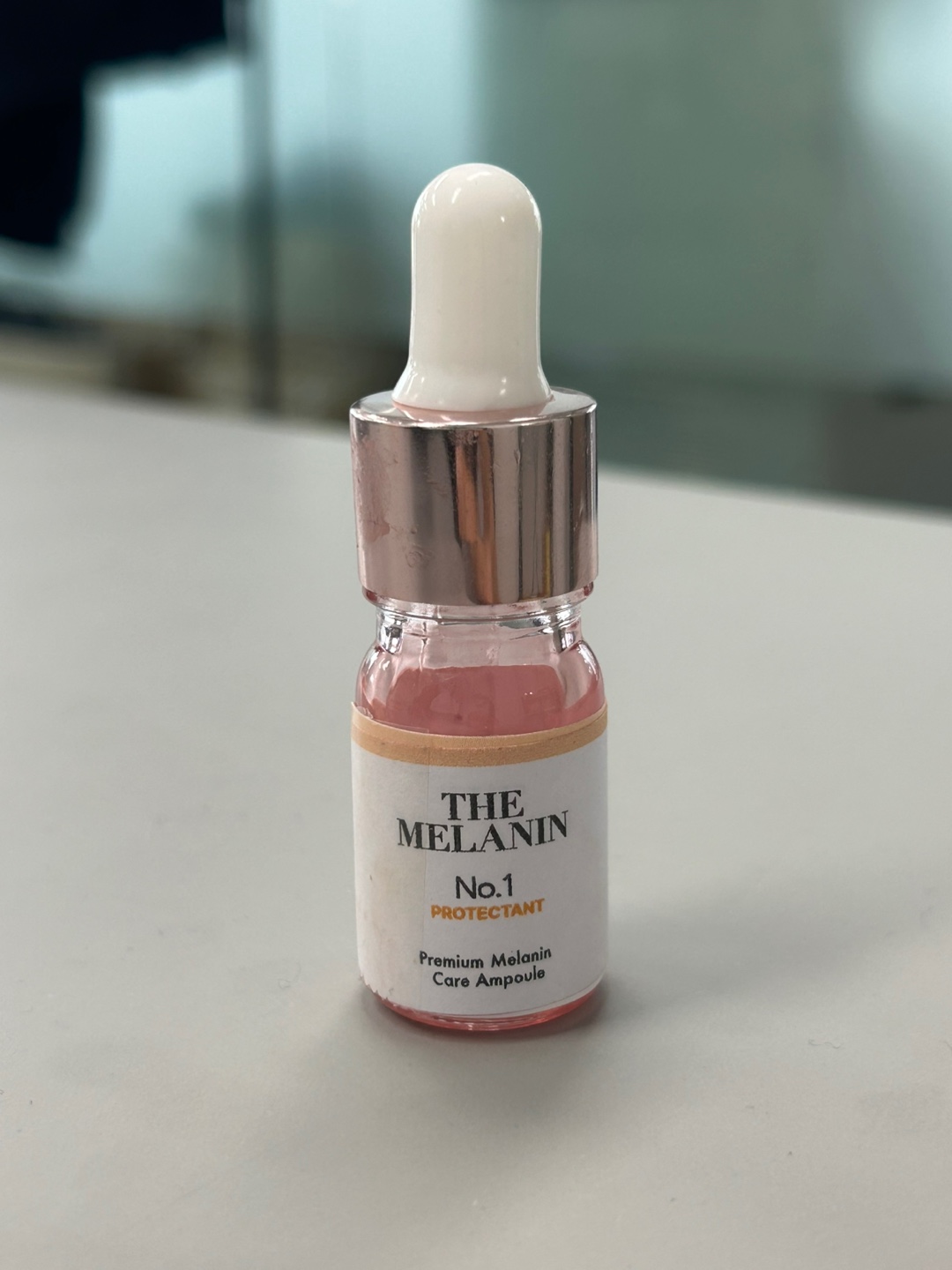 DRUG LABEL: The Melanin No.1 Protectant Premium Melanin Care Ampoule
NDC: 85514-6538 | Form: CREAM
Manufacturer: Reedfresh Co., LTD
Category: otc | Type: HUMAN OTC DRUG LABEL
Date: 20250428

ACTIVE INGREDIENTS: ALLANTOIN 1 g/100 g
INACTIVE INGREDIENTS: WATER 1 g/100 g

The Melanin No.1 Protectant Premium Melanin Care Ampoule

Active Ingredients

Allantoin

Inactive ingredients:

Purified Water, Glycerin, Niacinamide, Xanthan Gum, Echinacea purpurea Extract, 1,2-Hexanediol, Hydroxyacetophenone, Carbomer, Triethanolamine,
Lactobacillus Ferment, Sodium Hyaluronate, 1,2-Pentanediol, Dendrobium Nobile Stem Extract, Aloe Barbadensis Leaf Extract, Portulaca Oleracea Extract, Lycium Barbarum Fruit Extract, Sophora Flavescens Root Extract, Ethylhexylglycerin, Ergothioneine

PURPOSE

Temporarily protects and helps relieve minor skin irritations
Helps protect chapped or cracked skin

WARNINGS

For external use only
Do not use on deep or puncture wounds, animal bites, or serious burns unless directed by a doctor
Discontinue use and consult a dermatologist if any of the following symptoms occur, as continued use may worsen the condition: 1) Red spots, swelling, itching, or irritation during use; 2) Similar symptoms appearing on the applied area due to direct sunlight exposure
Avoid contact with eyes; if contact occurs, rinse immediately
Keep out of reach of children
Store in a cool, dry place, away from direct sunlight and extreme temperatures

These highlights do not include all the information needed to use. See full prescribing information.

Apply as needed

KEEP OUT OF THE REACH OF CHILDREN.

RECENT MAJOR CHANGES

Newly added

INDICATIONS AND USAGE

Temporarily protects and helps relieve minor skin irritations
Helps protect chapped or cracked skin